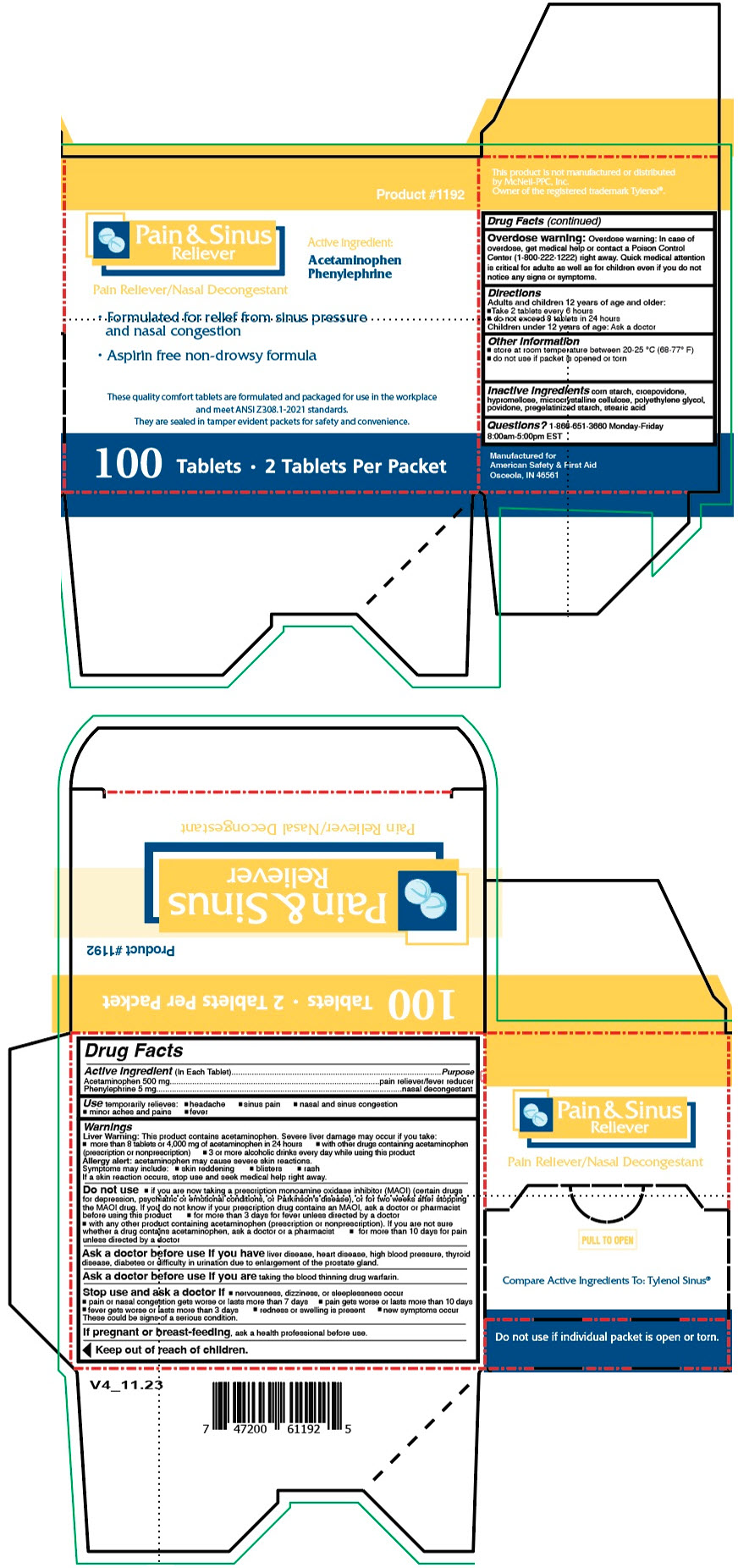 DRUG LABEL: Pain and Sinus
NDC: 73598-1192 | Form: TABLET
Manufacturer: JHK Inc dba American Safety & First Aid
Category: otc | Type: HUMAN OTC DRUG LABEL
Date: 20251216

ACTIVE INGREDIENTS: ACETAMINOPHEN 500 mg/1 1; PHENYLEPHRINE 5 mg/1 1
INACTIVE INGREDIENTS: STARCH, CORN; CROSPOVIDONE, UNSPECIFIED; HYPROMELLOSE, UNSPECIFIED; MICROCRYSTALLINE CELLULOSE; POLYETHYLENE GLYCOL, UNSPECIFIED; POVIDONE, UNSPECIFIED; STEARIC ACID

Pain & Sinus

Drug Facts

ACTIVE INGREDIENT

Active ingredient (In Each Tablet) | Purpose
Acetaminophen 500 mg | pain reliever/fever reducer
Phenylephrine 5 mg | nasal decongestant

Use

temporarily relieves:

- headache
- sinus pain
- nasal and sinus congestion
- minor aches and pains
- fever

Warnings

Liver Warning

This product contains acetaminophen. Severe liver damage may occur if you take:

- more than 8 tablets or 4,000 mg of acetaminophen in 24 hours
- with other drugs containing acetaminophen (prescription or nonprescription)
- 3 or more alcoholic drinks every day while using this product

Allergy alert: acetaminophen may cause severe skin reactions. Symptoms may include:

- skin reddening
- blisters
- rash

If a skin reaction occurs, stop use and seek medical help right away.

Do not use

- if you are now taking a prescription monoamine oxidase inhibitor (MAOI) (certain drugs for depression, psychiatric or emotional conditions, or Parkinson's disease), or for two weeks after stopping the MAOI drug. If you do not know if your prescription drug contains an MAOI, ask a doctor or pharmacist before using this product
- for more than 3 days for fever unless directed by a doctor
- with any other product containing acetaminophen (prescription or nonprescription). If you are not sure whether a drug contains acetaminophen, ask a doctor or a pharmacist
- for more than 10 days for pain unless directed by a doctor

Ask a doctor before use if you have liver disease, heart disease, high blood pressure, thyroid disease, diabetes or difficulty in urination due to enlargement of the prostate gland.

Ask a doctor before use if you are taking the blood thinning drug warfarin.

Stop use and ask a doctor if

- nervousness, dizziness, or sleeplessness occur
- pain or nasal congestion gets worse or lasts more than 7 days
- pain gets worse or lasts more than 10 days
- fever gets worse or lasts more than 3 days
- redness or swelling is present
- new symptoms occur

These could be signs of a serious condition.

PREGNANCY OR BREAST FEEDING

If pregnant or breast-feeding, ask a health professional before use.

Keep out of reach of children.

Overdose warning

Overdose warning: In case of overdose, get medical help or contact a Poison Control Center (1-800-222-1222) right away. Quick medical attention is critical for adults as well as for children even if you do not notice any signs or symptoms.

Directions

Adults and children 12 years of age and older:

- Take 2 tablets every 6 hours
- do not exceed 8 tablets in 24 hours

Children under 12 years of age: Ask a doctor

Other information

- store at room temperature between 20-25 °C (68-77° F)
- do not use if packet is opened or torn

Inactive ingredients

corn starch, crospovidone, hypromellose, microcrystalline cellulose, polyethylene glycol, povidone, pregelatinized starch, stearic acid

Questions?

1-866-651-3660 Monday-Friday 8:00am-5:00pm EST

PRINCIPAL DISPLAY PANEL - 100 Tablet Packet Box

Product #1192

Pain & Sinus
Reliever

Active ingredient:
Acetaminophen
Phenylephrine

Pain Reliever/Nasal Decongestant

- Formulated for relief from sinus pressure
  and nasal congestion
- Aspirin free non-drowsy formula

These quality comfort tablets are formulated and packaged for use in the workplace
and meet ANSI Z308.1-2021 standards.
They are sealed in tamper evident packets for safety and convenience.

100 Tablets • 2 Tablets Per Packet